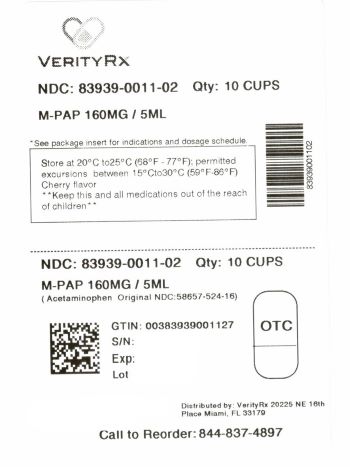 DRUG LABEL: M-PAP
NDC: 83939-0011 | Form: LIQUID
Manufacturer: VERITYRX, LLC
Category: otc | Type: HUMAN OTC DRUG LABEL
Date: 20251102

ACTIVE INGREDIENTS: ACETAMINOPHEN 160 mg/5 mL
INACTIVE INGREDIENTS: FD&C BLUE NO. 1; ANHYDROUS CITRIC ACID; FD&C RED NO. 40; HIGH FRUCTOSE CORN SYRUP; POLYETHYLENE GLYCOL, UNSPECIFIED; WATER; SODIUM BENZOATE; SACCHARIN SODIUM; SORBITOL; PROPYLENE GLYCOL

M-PAP

M-PAP

Acetaminophen Liquid

160 mg/5 mL

Pain Reliever / Fever Reducer

Sugar Free / Alcohol Free

Aspirin Free

CHERRY FLAVOR

Drug Facts

Active ingredient

(in each 5 mL teaspoonful)

Acetaminophen, USP 160 mg ....................

Purpose

Pain reliever/fever reducer

Uses

- reduces fever
- temporarily relieves minor aches and pains due to:
  - Headache
  - muscular aches
  - backache
  - arthritis
  - the common cold
  - toothache
  - menstrual cramps
  - reduces fever

Warnings

Liver Warning:This product contains acetaminophen.

Severe liver damage may occur if you take:

- more than 8 teaspoonfuls (40 mL) in 24 hours, which is the maximum daily amount
- with other drugs containing acetaminophen
- 3 or more alcoholic drinks every day while using this product

Allergy alert:Acetaminophen may cause severe skin reactions. Symptoms may include:

- skin reddening
- blisters
- rash

If a skin reaction occurs, stop use and seek medical help right away.

Sore throat warning

If sore throat is severe, persists for more than 2 days, is accompanied or followed by fever, headache, rash, nausea or vomiting, consult a doctor promptly.

Do not use

with any other drug containing acetaminophen (prescription or nonprescription). If you are not sure whether a drug contains acetaminophen, ask a doctor or pharmacist.

- for more than 10 days for pain unless directed by a doctor
- for more than 3 days for fever unless directed by a doctor
- if you are allergic to acetaminophen or any of the inactive ingredients in this product.

Ask a doctor before use

if you have health issues especially liver disease.

Ask a doctor or pharmacist before use

if you are taking other drugs, including the blood thinner warfarin.

Stop use and ask a doctor if

- new symptoms occur such as rash, hives, itching or hoarseness
- redness or swelling is present
- pain gets worse or lasts for more than 10 days
- fever gets worse or lasts for more than 3 days
- symptoms do not improve

These could be signs of a serious condition.

If pregnant or breast-feeding,

ask a health professional before use.

Keep out of reach of children. Overdose warning

Taking more than the recommended dose (overdose) may cause liver damage. In case of overdose, get medical help or contact a Poison Control Center right away. Prompt medical attention is critical even if you do not notice any signs or symptoms.

Directions

Do not exceed recommended dosage.

- adults and children 12 years of age and older:Take 3 teaspoonfuls (15 mL) every 5 hours; do not exceed 15 teaspoonfuls (75 mL) in 24 hours

- children under 12 years of age:Under the direct guidance of a licensed professional, doctor, or pharmacist.

Other Information

- each 5 mL contains:Sodium 3 mL

If dispensed, dispense in a tight, light resistant cotainer with a child-resistant cap. Store at 20°C to 25°C (68°F to 77°F), excursions permitted between 15°C and 30°C (between 59°F and 86°F).

Inactive Ingredients

Anhydrous citric acid, FD&C Blue #1, FD&C Red #40, flavor, high fructose corn syrup, polyethylene glycol, propylene glycol, purified water, saccharin sodium, sodium benzoate, sorbitol solution.

Questions?

Any adverse reactions contact FDA (888) 463-6332 or www.FDA.gov/medwatch

Distributed by:

VERITYRX, LLC

20225 NE 16th Place

Miami, FL 33179

PRINCIPAL DISPLAY PANEL

M-PAP
Acetaminophen Liquid
160 mg/5 mL
Cherry Flavor